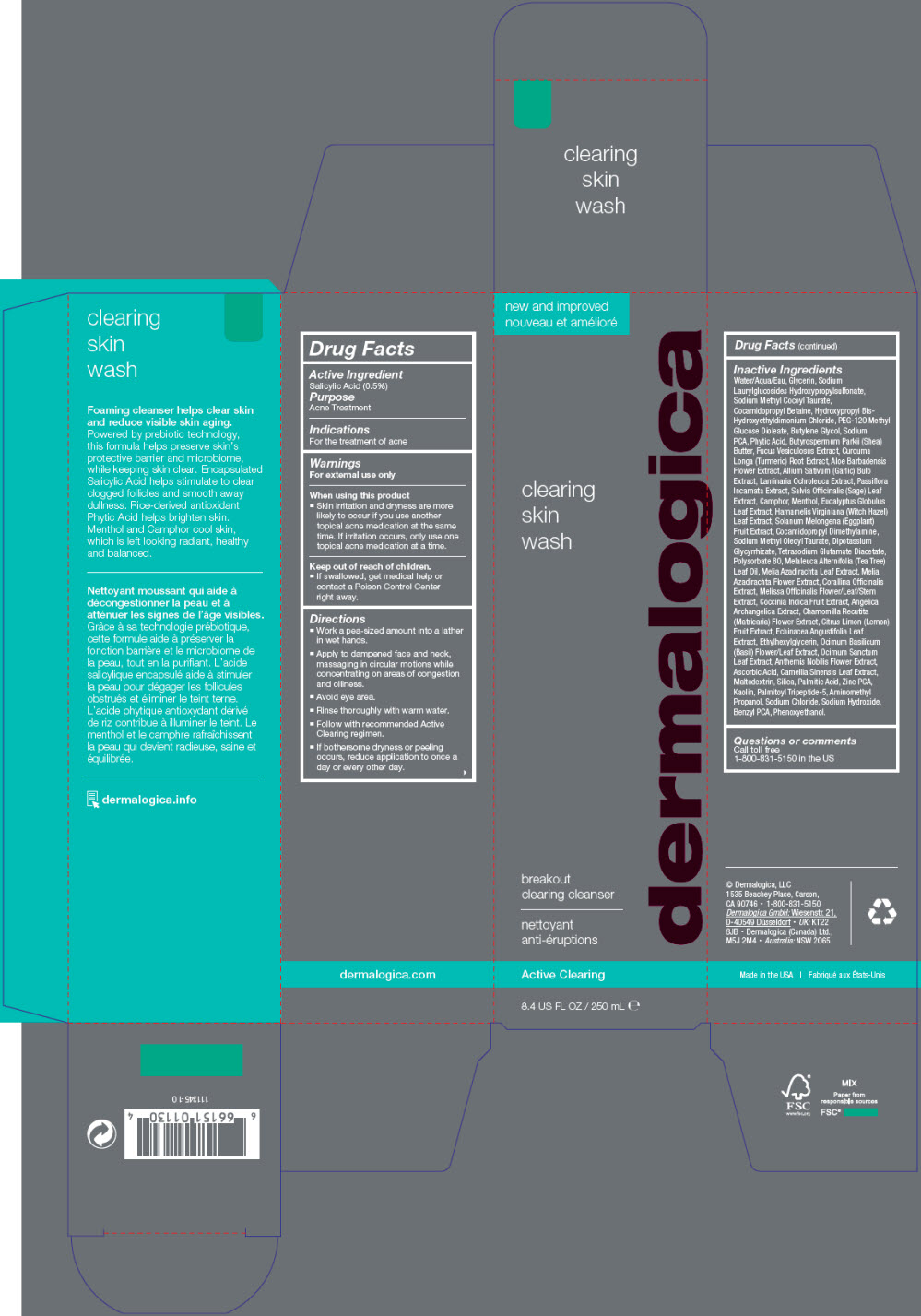 DRUG LABEL: Clearing Skin Wash
NDC: 68479-941 | Form: LIQUID
Manufacturer: Dermalogica, LLC
Category: otc | Type: HUMAN OTC DRUG LABEL
Date: 20220701

ACTIVE INGREDIENTS: Salicylic Acid 0.5 mg/100 mL
INACTIVE INGREDIENTS: Water; Glycerin; Sodium Laurylglucosides Hydroxypropylsulfonate; Sodium Methyl Cocoyl Taurate; Cocamidopropyl Betaine; Hydroxypropyl Bis-Hydroxyethyldimonium Chloride; PEG-120 Methyl Glucose Dioleate; Butylene Glycol; SODIUM PIDOLATE; Cocamidopropyl Dimethylamine; Sodium Methyl Oleoyl Taurate; Sodium Chloride; Phenoxyethanol; Benzyl PCA; FYTIC ACID; GLYCYRRHIZINATE DIPOTASSIUM; Tetrasodium Glutamate Diacetate; AMINOMETHYLPROPANOL; Polysorbate 80; CAMPHOR (NATURAL); LEVOMENTHOL; TEA TREE OIL; AZADIRACHTA INDICA LEAF; AZADIRACHTA INDICA FLOWER; CORALLINA OFFICINALIS; MELISSA OFFICINALIS WHOLE; COCCINIA GRANDIS WHOLE; GARLIC; MATRICARIA CHAMOMILLA WHOLE; CITRUS X LIMON WHOLE; ECHINACEA ANGUSTIFOLIA WHOLE; EUCALYPTUS GLOBULUS LEAF; WITCH HAZEL; LAMINARIA OCHROLEUCA; PASSIFLORA INCARNATA WHOLE; SAGE; ALOE; EGGPLANT; Ethylhexylglycerin; Sodium Hydroxide; TURMERIC; BASIL; OCIMUM TENUIFLORUM TOP; CHAMAEMELUM NOBILE WHOLE; Ascorbic Acid; SHEA BUTTER; GREEN TEA LEAF; Maltodextrin; SILICON DIOXIDE; FUCUS VESICULOSUS; Palmitic Acid; ZINC PIDOLATE; Kaolin; Palmitoyl Tripeptide-5

Clearing Skin Wash

Drug Facts

Active Ingredient

Salicylic Acid (0.5%)

Purpose

Acne Treatment

Indications

For the treatment of acne

Warnings

For external use only

When using this product

- Skin irritation and dryness are more likely to occur if you use another topical acne medication at the same time. If irritation occurs, only use one topical acne medication at a time.

Keep out of reach of children.

- If swallowed, get medical help or contact a Poison Control Center right away.

Directions

- Work a pea-sized amount into a lather in wet hands.
- Apply to dampened face and neck, massaging in circular motions while concentrating on areas of congestion and oiliness.
- Avoid eye area.
- Rinse thoroughly with warm water.
- Follow with recommended Active Clearing regimen.
- If bothersome dryness or peeling occurs, reduce application to once a day or every other day.

Inactive Ingredients

Water/Aqua/Eau, Glycerin, Sodium Laurylglucosides Hydroxypropylsulfonate, Sodium Methyl Cocoyl Taurate, Cocamidopropyl Betaine, Hydroxypropyl Bis-Hydroxyethyldimonium Chloride, PEG-120 Methyl Glucose Dioleate, Butylene Glycol, Sodium PCA, Phytic Acid, Butyrospermum Parkii (Shea) Butter, Fucus Vesiculosus Extract, Curcuma Longa (Turmeric) Root Extract, Aloe Barbadensis Flower Extract, Allium Sativum (Garlic) Bulb Extract, Laminaria Ochroleuca Extract, Passiflora Incarnata Extract, Salvia Officinalis (Sage) Leaf Extract, Camphor, Menthol, Eucalyptus Globulus Leaf Extract, Hamamelis Virginiana (Witch Hazel) Leaf Extract, Solanum Melongena (Eggplant) Fruit Extract, Cocamidopropyl Dimethylamine, Sodium Methyl Oleoyl Taurate, Dipotassium Glycyrrhizate, Tetrasodium Glutamate Diacetate, Polysorbate 80, Melaleuca Alternifolia (Tea Tree) Leaf Oil, Melia Azadirachta Leaf Extract, Melia Azadirachta Flower Extract, Corallina Officinalis Extract, Melissa Officinalis Flower/Leaf/Stem Extract, Coccinia Indica Fruit Extract, Angelica Archangelica Extract, Chamomilla Recutita (Matricaria) Flower Extract, Citrus Limon (Lemon) Fruit Extract, Echinacea Angustifolia Leaf Extract, Ethylhexylglycerin, Ocimum Basilicum (Basil) Flower/Leaf Extract, Ocimum Sanctum Leaf Extract, Anthemis Nobilis Flower Extract, Ascorbic Acid, Camellia Sinensis Leaf Extract, Maltodextrin, Silica, Palmitic Acid, Zinc PCA, Kaolin, Palmitoyl Tripeptide-5, Aminomethyl Propanol, Sodium Chloride, Sodium Hydroxide, Benzyl PCA, Phenoxyethanol.

Questions or comments

Call toll free 1-800-831-5150 in the US

PRINCIPAL DISPLAY PANEL - 250 mL Bottle Carton

new and improved

clearing
skin
wash

dermalogica

breakout
clearing cleanser

Active Clearing

8.4 US FL OZ / 250 mL ℮